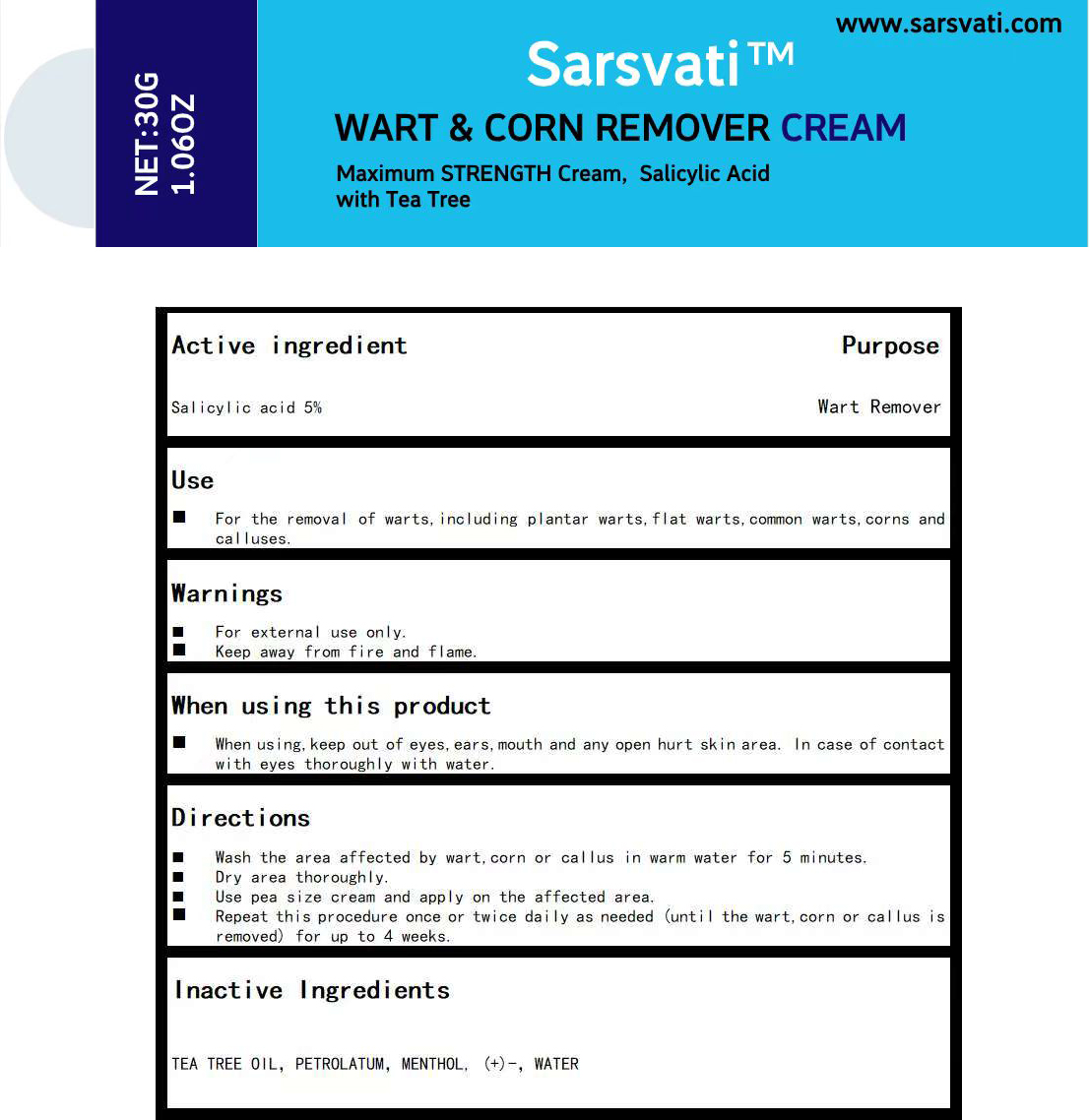 DRUG LABEL: Wart Corn Remover Cream
NDC: 85157-003 | Form: CREAM
Manufacturer: Shanghai Yijing Medical Technology Co., Ltd.
Category: otc | Type: HUMAN OTC DRUG LABEL
Date: 20250706

ACTIVE INGREDIENTS: SALICYLIC ACID 1.5 g/30 g
INACTIVE INGREDIENTS: TEA TREE OIL; WATER; PETROLATUM; MENTHOL, (+)-

85157-003 Wart & Corn Remover Cream

ACTIVE INGREDIENT

Salicylic Acid 5%

PURPOSE

Wart Remover

INDICATIONS AND USAGE

For the removal of warts, including plantar warts, flat warts, common warts, corns and calluses.

WARNINGS

For external use only.
Keep away from fire and flame.

WHEN USING

When using, keep out of eyes, ears, mouth and any open hurt skin area. In case of contact with eyes thoroughly with water

KEEP OUT OF REACH OF CHILDREN SECTION

DOSAGE AND ADMINISTRATION

Wash the area affected by wart,corn or callus in warm water for 5 minutes.
Dry area thoroughly.
Use pea size cream and apply on the affected area.
Repeat this procedure once or twice daily as needed (until the wart, corn or callus is removed)for up to4weeks.

INACTIVE INGREDIENT

WATER
MENTHOL, (+)-
TEA TREE OIL
PETROLATUM